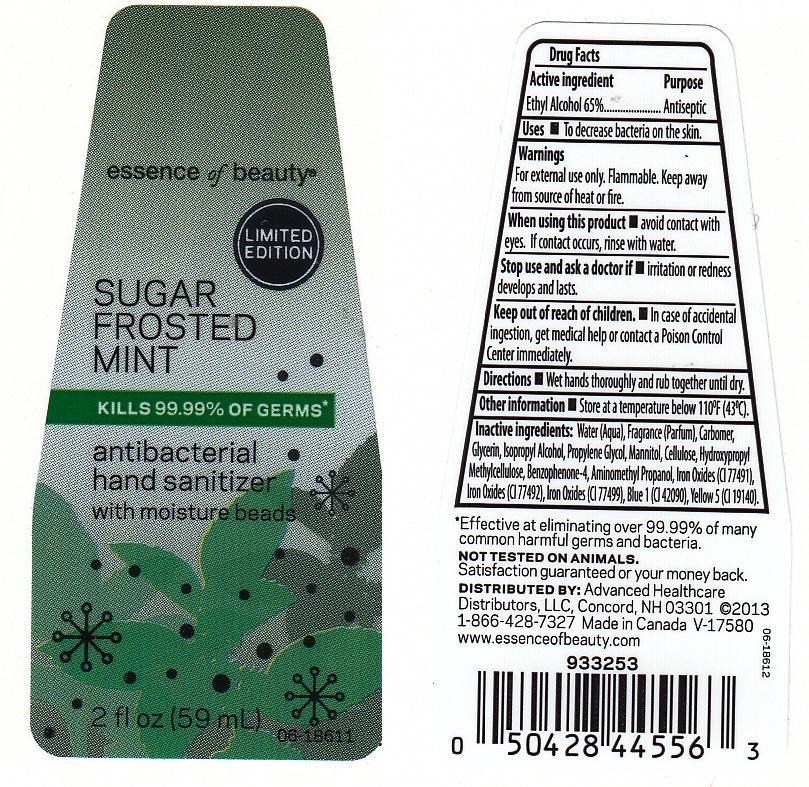 DRUG LABEL: ESSENCE OF BEAUTY
NDC: 59779-489 | Form: LIQUID
Manufacturer: CVS PHARMACY
Category: otc | Type: HUMAN OTC DRUG LABEL
Date: 20130708

ACTIVE INGREDIENTS: ALCOHOL 650 mg/1 mL
INACTIVE INGREDIENTS: WATER; CARBOMER 934; GLYCERIN; ISOPROPYL ALCOHOL; PROPYLENE GLYCOL; MANNITOL; POWDERED CELLULOSE; HYPROMELLOSES; SULISOBENZONE; AMINOMETHYLPROPANOL; FERRIC OXIDE RED; FERRIC OXIDE YELLOW; FERROSOFERRIC OXIDE; FD&C BLUE NO. 1; FD&C YELLOW NO. 5

DRUG FACTS

ACTIVE INGREDIENT

ETHYL ALCOHOL 65%

PURPOSE

ANTISEPTIC

USES

TO DECREASE BACTERIA ON THE SKIN.

WARNINGS

FOR EXTERNAL USE ONLY. FLAMMABLE. KEEP AWAY FROM SOURCE OF HEAT OR FIRE.

WHEN USING THIS PRODUCT

AVOID CONTACT WITH EYES. IF CONTACT OCCURS, RINSE WITH WATER.

STOP USE AND ASK A DOCTOR IF

IRRITATION OR REDNESS DEVELOPS AND LASTS.

KEEP OUT OF REACH OF CHILDREN

IN CASE OF ACCIDENTAL INGESTION, GET MEDICAL HELP OR CONTACT A POISON CONTROL CENTER IMMEDIATELY.

DIRECTIONS

WET HANDS THOROUGHLY AND RUB TOGETHER UNTIL DRY.

OTHER INFORMATION

STORE AT A TEMPERATURE BELOW 110F (43C).

INACTIVE INGREDIENTS:

WATER (AQUA), FRAGRANCE (PARFUM), CARBOMER, GLYCERIN, ISOPROPYL ALCOHOL, PROPYLENE GLYCOL, MANNITOL, CELLULOSE, HYDROXYPROPYL METHYLCELLULOSE, BENZOPHENONE-4, AMINOMETHYL PROPANOL, IRON OXIDES (CI 77491), IRON OXIDES (CI 77492), IRON OXIDES (CI 77499), BLUE 1 (CI 42090), YELLOW 5 (CI 19140).